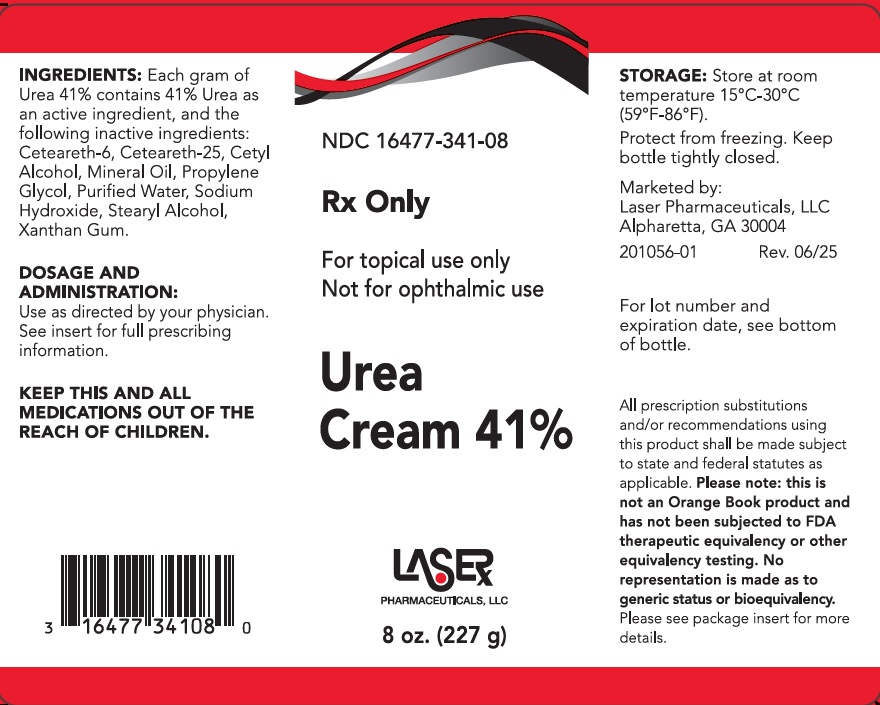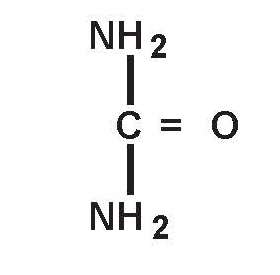 DRUG LABEL: Urea Cream 41%
NDC: 16477-341 | Form: CREAM
Manufacturer: Laser Pharmaceuticals, LLC
Category: prescription | Type: HUMAN PRESCRIPTION DRUG LABEL
Date: 20251106

ACTIVE INGREDIENTS: UREA 410 mg/1 g
INACTIVE INGREDIENTS: CETEARETH-25; CETYL ALCOHOL; STEARYL ALCOHOL; WATER; SODIUM HYDROXIDE; XANTHAN GUM; CETEARETH-6; MINERAL OIL; PROPYLENE GLYCOL

Urea Cream 41%

WARNINGS AND PRECAUTIONS

Urea Cream 41%

Rx Only For external use only. Not for ophthalmic use.

Description

Urea 41% is a keratolytic emollient which is a gentle, yet potent, tissue softener for nails and/or skin. Each gram of Urea 41% contains 41% urea as an active ingredient, and the following inactive ingredients: Ceteareth-6, Ceteareth-25, Cetyl Alcohol, Mineral Oil, Propylene Glycol, Purified Water, Sodium Hydroxide, Stearyl Alcohol, Xanthan Gum.

Urea is a diamide of carbonic acid with the following chemical structure:

Clinical Pharmacology

Urea gently dissolves the intracellular matrix which results in loosening of the horny layer of the skin and shedding of scaly skin at regular intervals, thereby softening hyperkeratotic areas of the skin.

Pharmacokinetics

The mechanism of action of topically applied urea is not yet known.

Indications and Usage

For debridement and promotion of normal healing of hyperkeratotic surface lesions, particularly where healing is retarded by local infection, necrotic tissue, fibrinous or purulent debris or eshar. Urea is useful for the treatment of hyperkeratotic conditions such as dry, rough skin, dermatitis, psoriasis, xerosis, ichthyosis, eczema, keratosis pilaris, keratosis palmaris, keratoderma, corns and calluses, as well as damaged, ingrown and devitalized nails.

Contraindications

Known hypersensitivity to any of the listed ingredients.

Warnings

For topical use only. Avoid contact with eyes, lips or mucous membranes.

Precautions

This medication is to be used as directed by a physician and should not be used to treat any condition other than that for which it was prescribed. If redness or irritation occurs, discontinue use and consult a physician.

PREGNANCY

PREGNANACY: Pregnancy Category B. Animal reproduction studies have revealed no evidence of harm to the fetus, however, there are no adequate and well-controlled studies in pregnant women. Because animal reproductive studies are not always predictive of human response, Urea 41% should be given to a pregnant woman only if clearly needed.

NURSING MOTHERS

NURSING MOTHERS: It is not known whether or not this drug is excreted in human milk. Because many drugs are excreted in human milk, caution should be exercised when Urea 41% is administered to a nursing woman.

Adverse Reactions

Transient stinging, burning, itching or irritation may occur and normally disappear upon discontinuing the medication.

Dosage and Administration

Apply Urea 41% to affected skin twice per day, or as directed by your physician. Rub in until completely absorbed.

Apply to diseased or damaged nail(s) twice per day, or as directed by a physician.

All prescription substitutions and/or recommendations using this product shall be made subject to state and federal statutes as applicable. Please note: this is not an Orange Book product and has not been subjected to FDA therapeutic equivalency or other equivalency testing. No representation is made as to generic status or bioequivalency. Each person recommending a prescription substitution using this product shall make such recommendations based on each person's professional opinion and knowledge, upon evaluating the active ingredients, excipients, inactive ingredients and chemical information provided herein.

How Supplied

Urea 41% Cream 8 oz.(227 g): NDC 16477-341-08

Store at room temperature 15°C - 30°C (59°F - 86°F). Protect from freezing. Keep bottle tightly
closed.

KEEP OUT OF REACH OF CHILDREN

KEEP THIS AND ALL MEDICATIONS OUT OF THE REACH OF CHILDREN.

Marketed by:
Laser Pharmaceuticals, LLC
1015 Nine North Drive, Suite 400
Alpharetta, GA 30004
1-844-302-5227

PACKAGE LABEL

NDC 16477-341

Rx Only

For topical use only

Not for ophthalmic use

Urea Cream 41%

LASER PHARMACEUTICALS, LLC